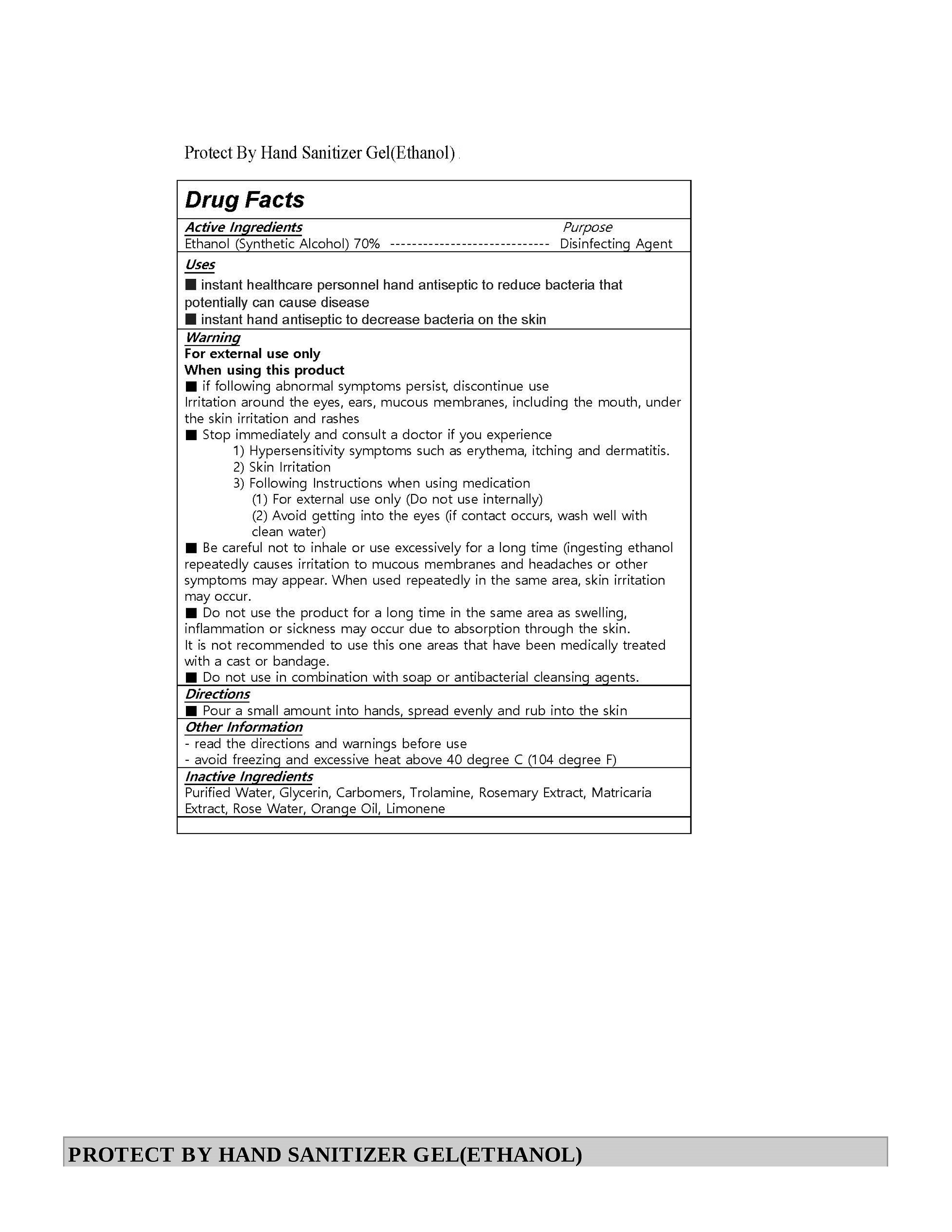 DRUG LABEL: Protect By Hand Sanitizer gel (ethanol)
NDC: 80594-0001 | Form: GEL
Manufacturer: Ken Company Co., Ltd.
Category: otc | Type: HUMAN OTC DRUG LABEL
Date: 20200914

ACTIVE INGREDIENTS: ALCOHOL 70 mL/100 mL
INACTIVE INGREDIENTS: LIMONENE, (+)-; TROLAMINE; ROSEMARY OIL; MATRICARIA RECUTITA; GLYCERIN; ORANGE OIL; CARBOMER 940; WATER

Drug Facts

ACTIVE INGREDIENT

alcohol

INACTIVE INGREDIENT

Water
Glycerin
Carbomer
Triethanolamine
Rosmarinus Officinalis (Rosemary) Leaf Extract
Chamomilla Recutita (Matricaria) Flower Extract
Rose Centifolia Flower Water
Citrus Aurantium Dulcis (Orange) Oil
Limonene

PURPOSE

Sterilization of hands and skin

KEEP OUT OF REACH OF THE CHILDREN

INDICATIONS AND USAGE

Apply an appropriate amount on your hands and rub well to dry.

WARNINGS

1. Do not use on the following body parts. A wide range of body parts and damaged skin around the eyes and
ears, in the oral cavity (may have irritating effects)
2. If the following symptoms appear, stop using them immediately and consult a doctor or pharmacist.
1) Hypersensitivity symptoms such as rash, erythema, itching, and edema
2) Skin irritation symptoms
3. Other precautions
1) For external use only (do not underwear).
2) Be careful not to get into your eyes, and if so, rinse well with clean water and consult a doctor or pharmacist.
3) Be careful not to inhale the vapor when using it extensively or for a long period of time (irritation to the
mucous membranes, headaches, etc. may occur if ethanol vapor is consumed in large quantities or repeatedly).
4) If repeated use on the same site, be careful as the skin may become rough due to degreasing.
5) Do not use sealed bandages, cast bandages, packs, etc., as irritation may occur.
6) Do not use this medicine for anal or vaginal compresses as it may cause irritation or chemical burns.
7) Do not use for any other purpose.
4. Precautions for storage
1) Avoid shading and keep in shading.
2) Keep it out of reach of children, and if a child swallows it, go to the hospital right away.
3) After use, close the product completely with a lid to prevent the product from drying out or entering foreign
Objects.

DOSAGE AND ADMINISTRATION

for external use only